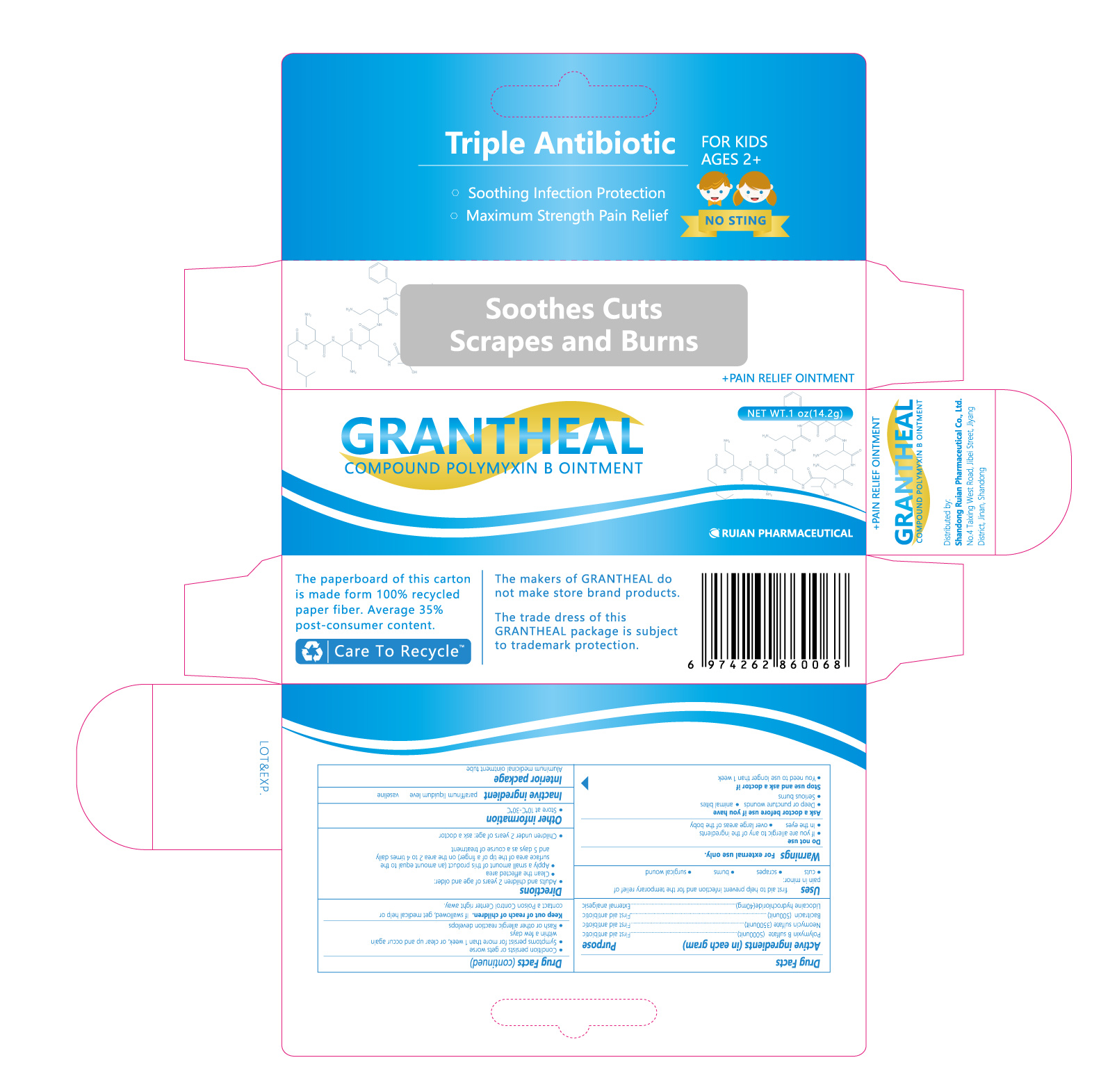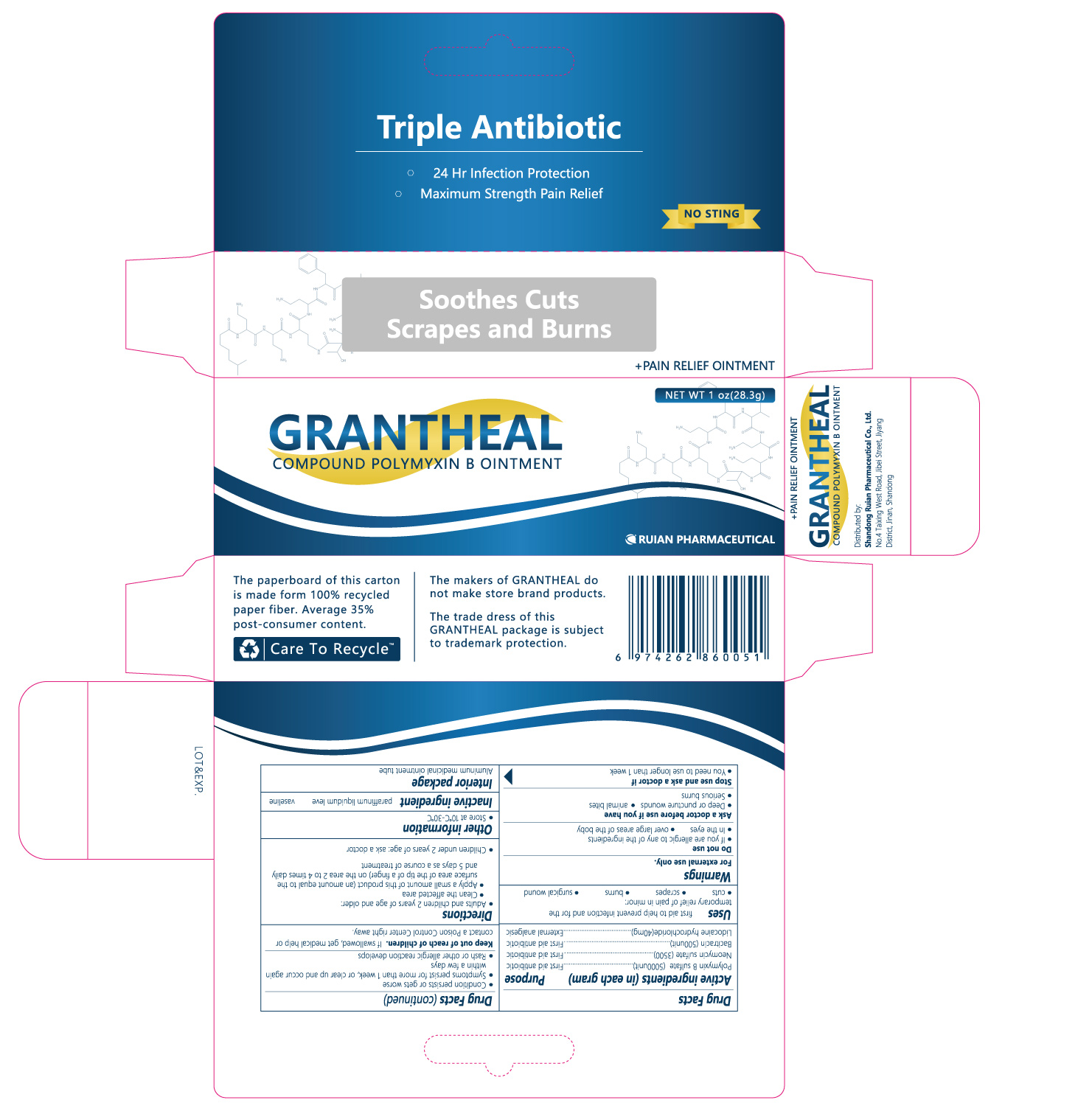 DRUG LABEL: Triple Antibiotic
NDC: 82199-530 | Form: OINTMENT
Manufacturer: Shandong Ruian Pharmaceutical Co.,Ltd.
Category: otc | Type: HUMAN OTC DRUG LABEL
Date: 20211113

ACTIVE INGREDIENTS: POLYMYXIN B SULFATE 5000 [USP'U]/1 g; NEOMYCIN SULFATE 3500 [USP'U]/1 g; BACITRACIN 500 [USP'U]/1 g; LIDOCAINE 40 mg/1 g
INACTIVE INGREDIENTS: PETROLATUM

WARNINGS

For external use only.

INACTIVE INGREDIENT

white petrolatum

DO NOT USE

• if you are allergic to any of the ingredients
• in the eyes
• over large areas of the body

KEEP OUT OF REACH OF CHILDREN

If swallowed, get medical help or contact a Poison Control Center right away

PURPOSE

First aid antibiotic
External analgesic

ASK DOCTOR

• deep or puncture wounds
• animal bites
• serious burns

ACTIVE INGREDIENT

POLYMYXIN B SULFATE;
NEOMYCIN SULFATE;
BACITRACIN ZINC;
PRAMOXINE HYDROCHLORIDE

OTHER SAFETY INFORMATION

store at 10-30°C

DOSAGE AND ADMINISTRATION

• adults and children 2 years of age or older:
• clean the affected area
• apply a small amount of this product (an amount equal to the surface area of the tip of a finger) on the area 1 to 3 times daily
• may be covered with a sterile bandage
• children under 2 years of age: ask a doctor

INDICATIONS AND USAGE

first aid to help prevent infection and for temporary relief of pain or discomfort in minor:
• cuts
• scrapes
• burns

PACKAGE LABEL

NDC:82199-530-12 28.3 g in 1 TUBE

NDC:82199-530-11 14.2 g in 1 TUBE